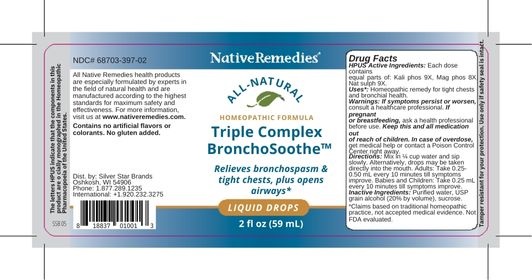 DRUG LABEL: NativeRemedies Triple Complex BronchoSoothe
NDC: 68703-397 | Form: LIQUID
Manufacturer: Silver Star Brands
Category: homeopathic | Type: HUMAN OTC DRUG LABEL
Date: 20250101

ACTIVE INGREDIENTS: POTASSIUM PHOSPHATE, DIBASIC 9 [hp_X]/59 mL; MAGNESIUM PHOSPHATE, DIBASIC TRIHYDRATE 8 [hp_X]/59 mL; SODIUM SULFATE 9 [hp_X]/59 mL
INACTIVE INGREDIENTS: WATER; SUCROSE; ALCOHOL

NativeRemedies® Triple Complex BronchoSoothe™

HPUS Active Ingredients: Each dose contains equal parts of: Kali phos 9X, Mag phos 8X, Nat sulph 9X.

The letters HPUS indicate that the components in this product are officially monographed in the Homeopathic Pharmacopoeia of the United States.

Uses*

Uses*: Homeopathic remedy for tight chests and bronchial health.

*Claims based on traditional hoemopatic practice, not accepted medical evidence. Not FDA evaluated.

Warnings

Warnings: If symptoms persist or worsen, consult a helathcare professional. If pregnant or breastfeeding, ask a health professional before use. Keep this and all medication out of reach of children. In case of overdose, get medical help or contact a Poison Control Center right away.

Directions

Directions: Mix in 1/4 cup water and sip slowly. Alternatively, drops may be taken directly into the mouth. Adults: Take 0.25-0.50 mL every 10 minutes till symptoms improve. Babies and Children: Take 0.25 mL every 10 minutes till symptoms imporve.

OTHER SAFETY INFORMATION

Contains no artificial flavors or colorants. No gluten added.

Tamper resistant for your protection. Use only if safety seal is intact.

Inactive Ingredients

Inactive Ingredients: Purified water, USP grain alcohol (20% by volume), sucrose.

KEEP OUT OF REACH OF CHILDREN

Keep this and all medication out of reach of children. In case of overdose, get medical help or contact a Poison Control Center right away.

PREGNANCY OR BREAST FEEDING

If pregnant or breastfeeding, ask a health professional before use.

PURPOSE

Relieves bronchospasm & tight chests, plus opens airways.